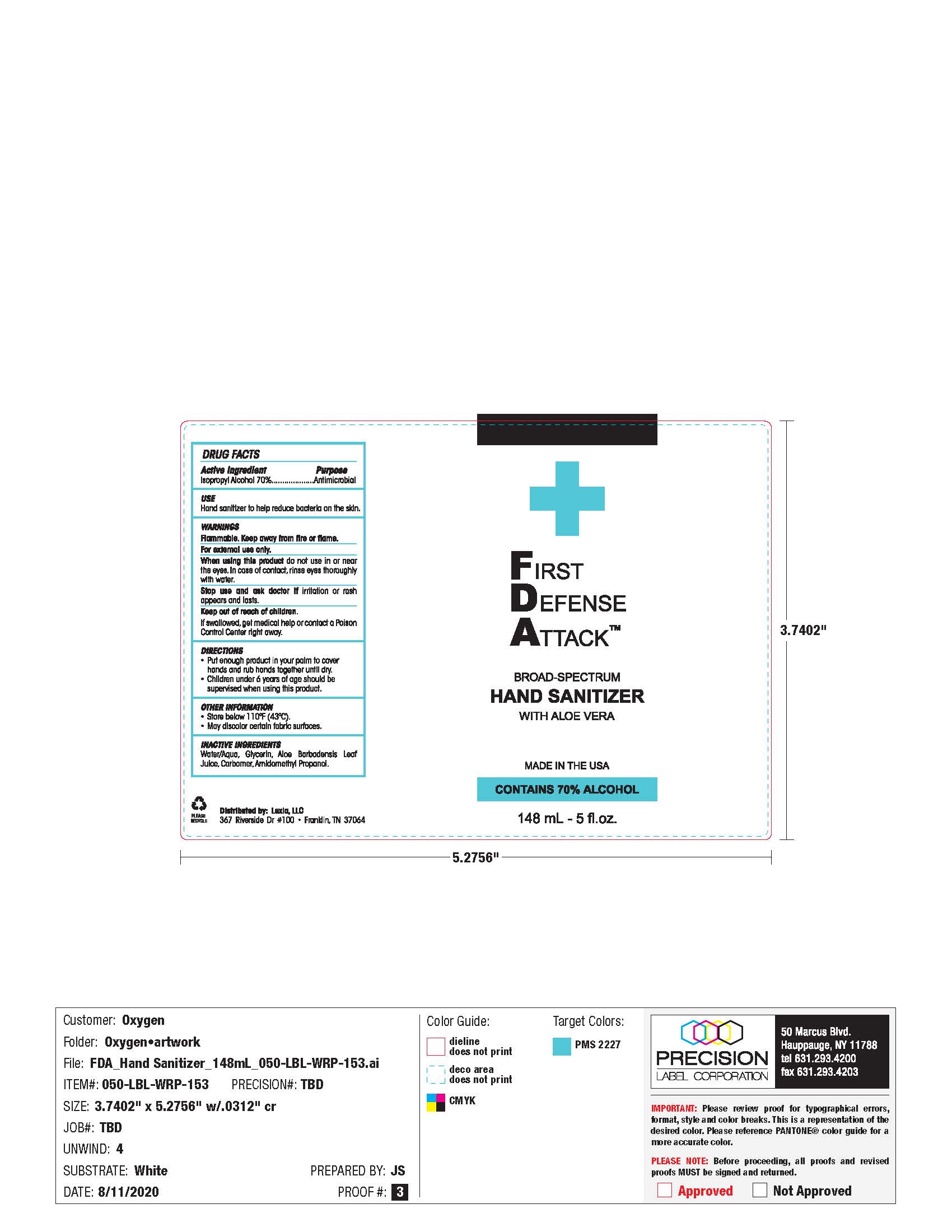 DRUG LABEL: Hand Sanitizer
NDC: 61354-023 | Form: GEL
Manufacturer: Oxygen development LLC
Category: otc | Type: HUMAN OTC DRUG LABEL
Date: 20210218

ACTIVE INGREDIENTS: ISOPROPYL ALCOHOL 70 mL/100 mL
INACTIVE INGREDIENTS: GLYCERIN 1.49 mL/100 mL; CARBOMER 940 0.5 mL/100 mL; WATER 26.98 mL/100 mL

FIRST DEFENSE ATTACK BROAD-SPECTRUM HAND SANITIZER WITH ALOE VERA

Active Ingredient

Isopropyl Alcohol 70%. Purpose: Antimicrobial

Purpose

Antimicrobial.

Use

Hand Sanitizer to help reduce bacteria on the skin.

Warnings

Flammable. Keep away from fire or flame.

For external use only.

When using this product do not use in or near the eyes. In case of contact, rinse eyes thoroughly with water.

Stop use and ask a doctor if irritation or rash appears and lasts.

KEEP OUT OF REACH OF CHILDREN

If swallowed, get medical help or contact a Poison Control Center right away.

Directions

Put enough product in your palm to cover hands and rub hands together until dry.

Children under 6 years of age should be supervised when using this product.

Other information

Store below 110°F (43°C)

May discolor certain fabric surfaces.

Inactive ingredients

Water/Agua, Glycerin, Aloe Barbadensis Leaf Juice, Carbomer, Amidomethyl Propanol

Package Label - Principal Display Panel

148 ml NDC: 61354-023-01